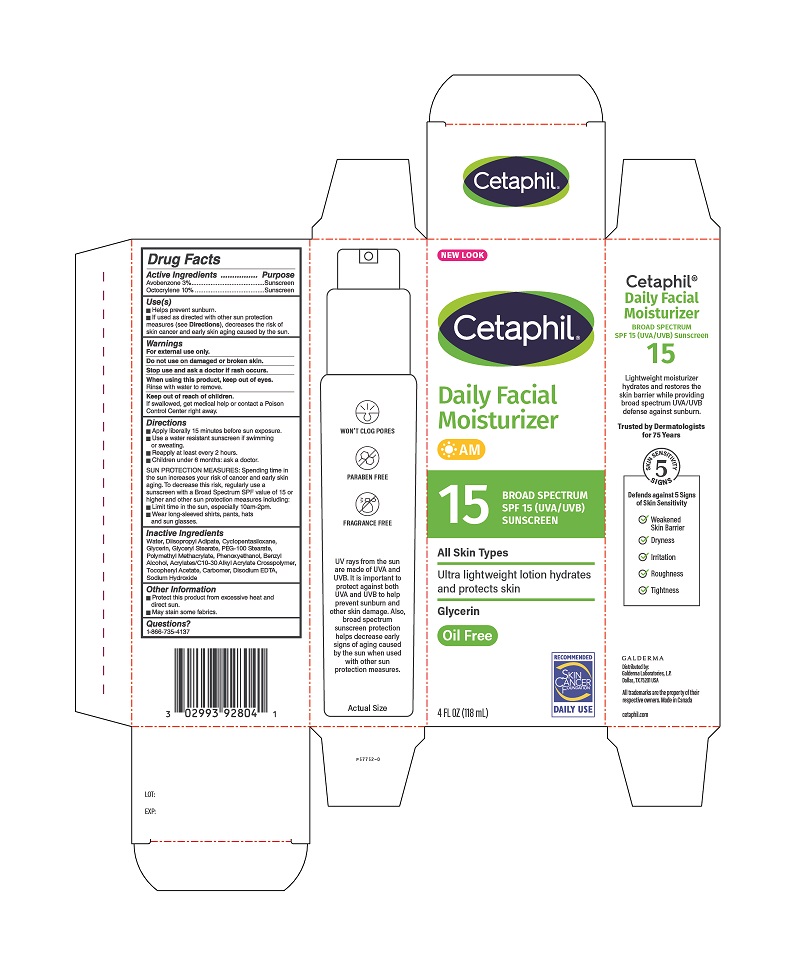 DRUG LABEL: Cetaphil
NDC: 0299-3928 | Form: LOTION
Manufacturer: Galderma Laboratories, L.P.
Category: otc | Type: HUMAN OTC DRUG LABEL
Date: 20240416

ACTIVE INGREDIENTS: OCTOCRYLENE 10 g/100 mL; AVOBENZONE 3 g/100 mL
INACTIVE INGREDIENTS: WATER; DIISOPROPYL ADIPATE; Cyclomethicone 5; GLYCERIN; GLYCERYL MONOSTEARATE; PEG-100 STEARATE; Poly(Methyl Methacrylate; 450000 Mw); Phenoxyethanol; Benzyl Alcohol; Acrylates/C10-30 Alkyl Acrylate Crosspolymer (60000 Mpa.S); .Alpha.-Tocopherol Acetate; Carbomer Homopolymer, Unspecified Type; Edetate Disodium; Sodium Hydroxide

Cetaphil® Daily Facial Moisturizer

ACTIVE INGREDIENT

Avobenzone 3%
Octocrylene 10%

PURPOSE

Sunscreen

USE(S)

- Helps prevent sunburn
- If used as directed with other sun protection measures (see Directions) decreases the risk of skin cancer and early skin aging caused by the sun.

WARNINGS

For external use only
Do not use on damaged or broken skin.
Stop use and ask a doctor if rash occurs.
When using this product keep out of eyes.
Rinse with water to remove.

Keep out of reach of children.

If swallowed, get medical help or contact a Poison Control Center right away.

DIRECTIONS

- Apply liberally 15 minutes before sun exposure.
- Use a water resistant sunscreen if swimming or sweating.
- Reapply at least every 2 hours.
- Children under 6 months: ask a doctor.
  SUN PROTECTION MEASURES: Spending time in the sun increases your risk of cancer and early skin aging. To decrease this risk, regularly use a sunscreen with a Broad Spectrum SPF value of 15 or higher and other sun protection measures including:
- Limit time in the sun, especially 10am - 2pm.
- Wear long-sleeved shirts, pants, hats and sun glasses.

INACTIVE INGREDIENTS:

Water, Diisopropyl Adipate, Cyclopentasiloxane, Glycerin, Glyceryl Stearate, PEG-100 Stearate, Polymethyl Methacrylate, Phenoxyethanol, Benzyl Alcohol, Acrylates/C10-30 Alkyl Acrylate Crosspolymer, Tocopheryl Acetate, Carbomer, Disodium EDTA, Sodium Hydroxide

Other Information

• Protect this product from excessive heat and direct sun.
• May stain some fabrics.

Questions?

1-866-735-4137

PRINCIPAL DISPLAY PANEL - 4 FL OZ Carton

NEW LOOK
Cetaphil®

Daily Facial
Moisturizer
AM

15 BROAD SPECTRUM
SPF 15 (UVA/UVB)
SUNSCREEN

All Skin Types

Ultra lightweight lotion hydrates
and protects skin

Glycerin
Oil-Free

Recommended
Skin Cancer Foundation
Daily Use

4 FL OZ (118 mL)

Distributed by:
Galderma Laboratories, L.P.
Dallas, TX 75201 USA

All trademarks are the property of their respective owners.

Made in Canada

cetaphil.com
P57752-0